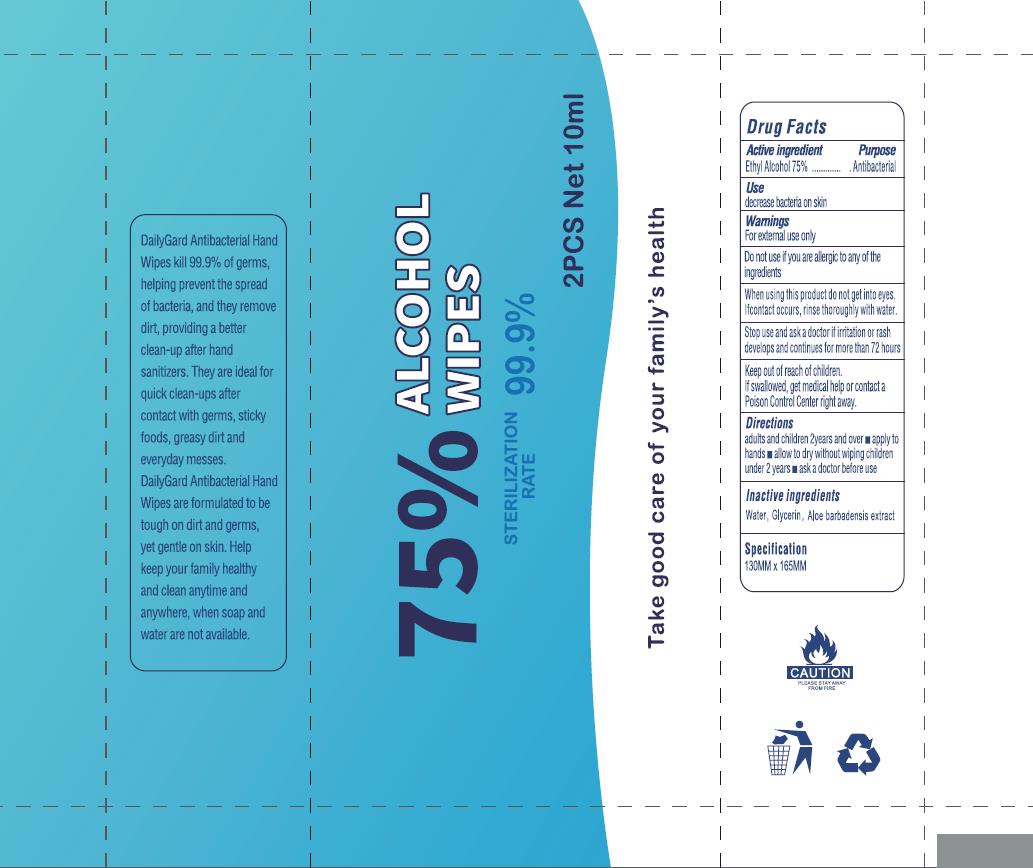 DRUG LABEL: ALCOHOL WIPES
NDC: 75749-051 | Form: CLOTH
Manufacturer: Ningbo Pretty Tourism Manufacture Co., Ltd
Category: otc | Type: HUMAN OTC DRUG LABEL
Date: 20200811

ACTIVE INGREDIENTS: ALCOHOL 75 mL/100 mL
INACTIVE INGREDIENTS: GLYCERIN; WATER; ALOE

Active Ingredient

Ethyl Alcohol 75%

Purpose

Anitbacterial

Use

decrease bacteria on skin

Warnings

For external use only.

Do not use

If you are allergic to any of the ingredients

When using this product keep out of eyes, ears, and mouth. In case of contact with eyes, rinse eyes thoroughly with water.

Stop use and ask a doctor if irritation or rash occurs develops and continues for more than 72 hours

Keep out of reach of children. If swallowed, get medical help or contact a Poison Control Center right away.

Directions

adult and children 2years and over

- apply to hands
- allow to dry without wiping

children under 2 years

- ask a doctor before use

Inactive ingredients

Water

Glycerin

Aloe barbadensis extract